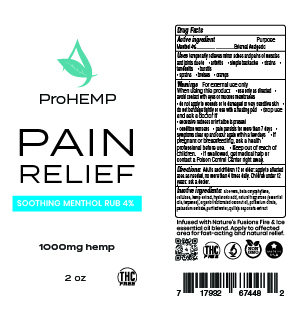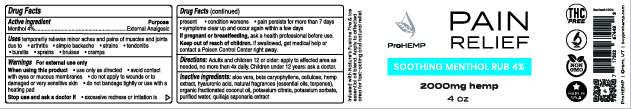 DRUG LABEL: ProHEMP Soothing Menthol Rub 4%
NDC: 73769-100 | Form: CREAM
Manufacturer: NATURE'S FUSIONS, LLC
Category: otc | Type: HUMAN OTC DRUG LABEL
Date: 20220131

ACTIVE INGREDIENTS: MENTHOL 4 g/60 mL
INACTIVE INGREDIENTS: ALOE VERA LEAF; .BETA.-CARYOPHYLLENE ALCOHOL; POWDERED CELLULOSE; HYALURONATE SODIUM; QUILLAJA SAPONARIA BARK; FRAGRANCE 13576; POTASSIUM CITRATE; HEMP; CAPRYLIC/CAPRIC/LAURIC TRIGLYCERIDE; POTASSIUM SORBATE; WATER

ProHEMP Pain Relief Soothing Menthol Rub 4%

PURPOSE

temporarily relieves minor aches and pains of muscles and joints due to • arthritis • simple backache • strains • tendonitis • bursitis • sprains • bruises • cramps

ACTIVE INGREDIENT

Menthol 4% - External Analgesic

Keep out of reach of children. • If swallowed, get medical help or contact a Poison Control Center right away.

INDICATIONS AND USAGE

Adults and children 12 or older: apply to affected area as needed, no more than 4 times daily. Children under 12 years: ask a doctor.

INACTIVE INGREDIENT

aloe vera, beta caryophyllene, cellulose, hemp extract, hyaluronic acid, natural fragrances (essential oils, terpenes), organic fractionated coconut oil, potassium citrate, potassium sorbate, purified water, quillaja saponaria extract

DOSAGE AND ADMINISTRATION

Adults and children 12 or older: apply to affected area as needed, no more than 4 times daily. Children under 12 years: ask a doctor.

WARNINGS

For external use only

When using this product

• use only as directed • avoid contact with eyes or mucous membranes • do not apply to wounds or to damaged or very sensitive skin • do not bandage tightly or use with a heating pad • Stop use and ask a doctor if • excessive redness or irritation is present • condition worsens • pain persists for more than 7 days • symptoms clear up and occur again within a few days • If pregnant or breastfeeding, ask a health professional before use. • Keep out of reach of children. • If swallowed, get medical help or contact a Poison Control Center right away.

PACKAGE LABEL

4 oz jar display panel